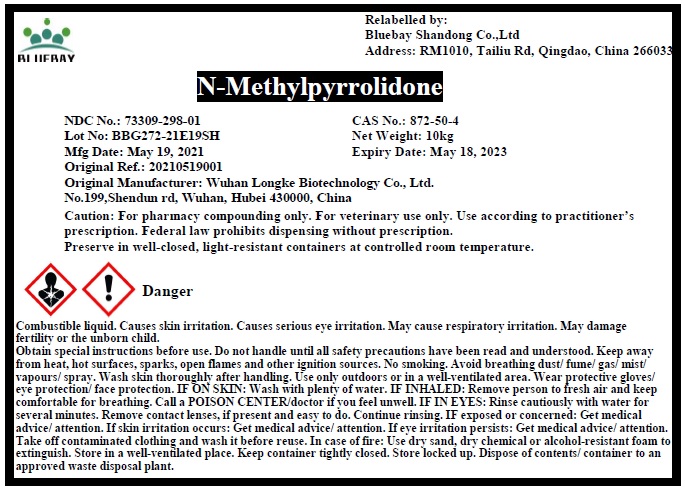 DRUG LABEL: N-methylpyrrolidone
NDC: 73309-298 | Form: LIQUID
Manufacturer: BLUEBAY SHANDONG CO.,LTD
Category: other | Type: BULK INGREDIENT
Date: 20210528

ACTIVE INGREDIENTS: METHYLPYRROLIDONE 1 kg/1 kg

N-methylpyrrolidone